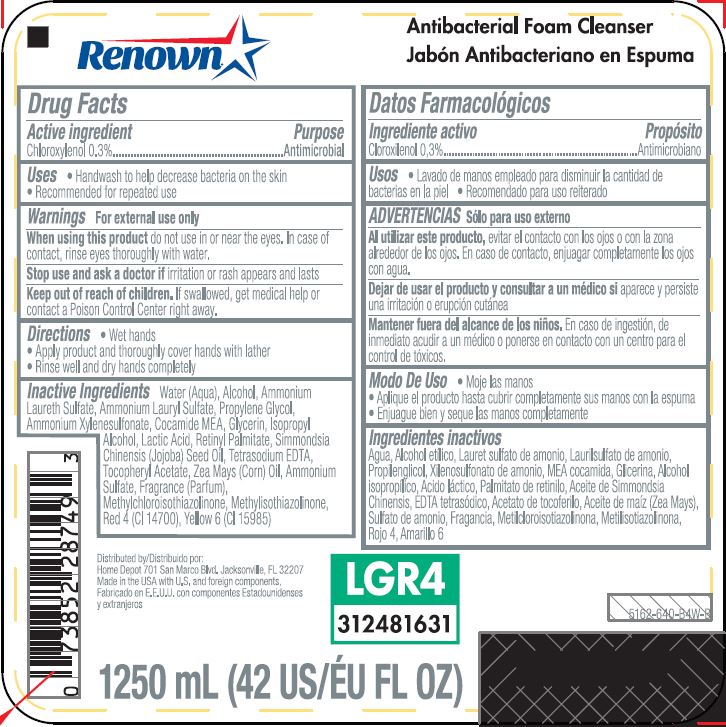 DRUG LABEL: RENOWN Antibacterial Foam Cleanser
NDC: 42584-0081 | Form: LIQUID
Manufacturer: Home Depot U.S.A., Inc.
Category: otc | Type: HUMAN OTC DRUG LABEL
Date: 20260113

ACTIVE INGREDIENTS: CHLOROXYLENOL 0.3 mg/100 mL
INACTIVE INGREDIENTS: WATER; ALCOHOL; AMMONIUM LAURETH-2 SULFATE; AMMONIUM LAURYL SULFATE; PROPYLENE GLYCOL; AMMONIUM XYLENESULFONATE; COCO MONOETHANOLAMIDE; GLYCERIN; ISOPROPYL ALCOHOL; LACTIC ACID; VITAMIN A PALMITATE; JOJOBA OIL; EDETATE SODIUM; .ALPHA.-TOCOPHEROL ACETATE, D-; CORN OIL; AMMONIUM SULFATE; METHYLCHLOROISOTHIAZOLINONE; METHYLISOTHIAZOLINONE; FD&C RED NO. 4; FD&C YELLOW NO. 6

RENOWN Antibacterial Foam Cleanser

Active ingredient

Chloroxylenol 0.3%

Purpose

Antimicrobial

Uses

- Handwash to help decrease bacteria on the skin
- Recommended for repeated use

Warnings

For external use only

WHEN USING

When using this productdo not use in or near the eyes. In case of contact, rinse eyes thoroughly with water.

Stop use and ask a doctor ifirritation or rash appears and lasts

Keep out of reach of children.If swallowed, get medical help or contact a Poison Control Center right away.

Directions

- Wet hands
- Apply a small amount of product and work into a lather
- Rinse well and dry hands completely

Inactive ingredients

Water (Aqua), Alcohol, Ammonium Laureth Sulfate, Ammonium Lauryl Sulfate, Propylene Glycol, Ammonium Xylenesulfonate, Cocamide MEA, Glycerin, Isopropyl Alcohol, Lactic Acid, Retinyl Palmitate, Simmondsia Chinensis (Jojoba) Seed Oil, Tetrasodium EDTA, Tocopheryl Acetate, Zea Mays (Corn) Oil, Ammonium Sulfate, Fragrance (Parfum), Methylchloroisothiazolinone, Methylisothiazolinone, Red 4 (CI 14700), Yellow 6 (CI 15985)